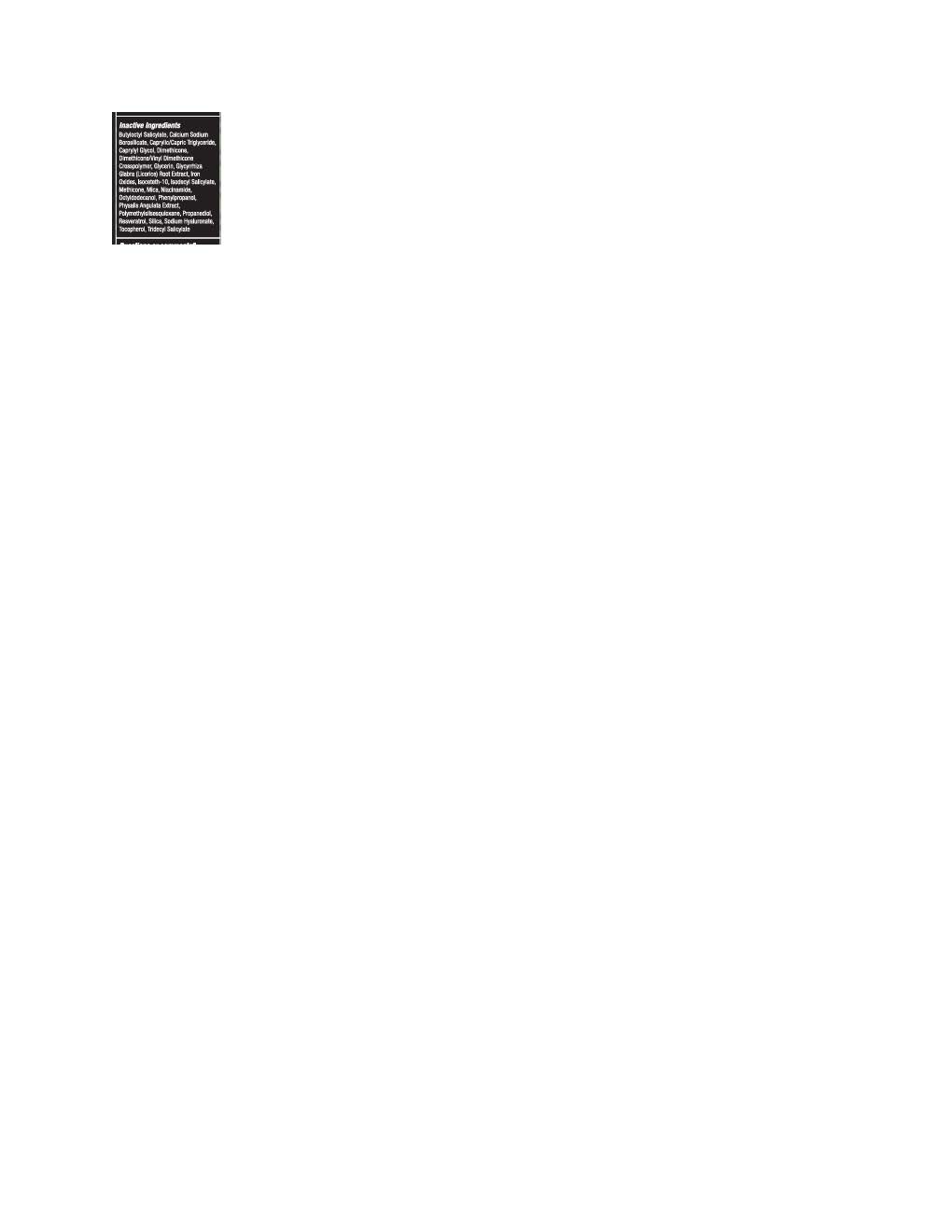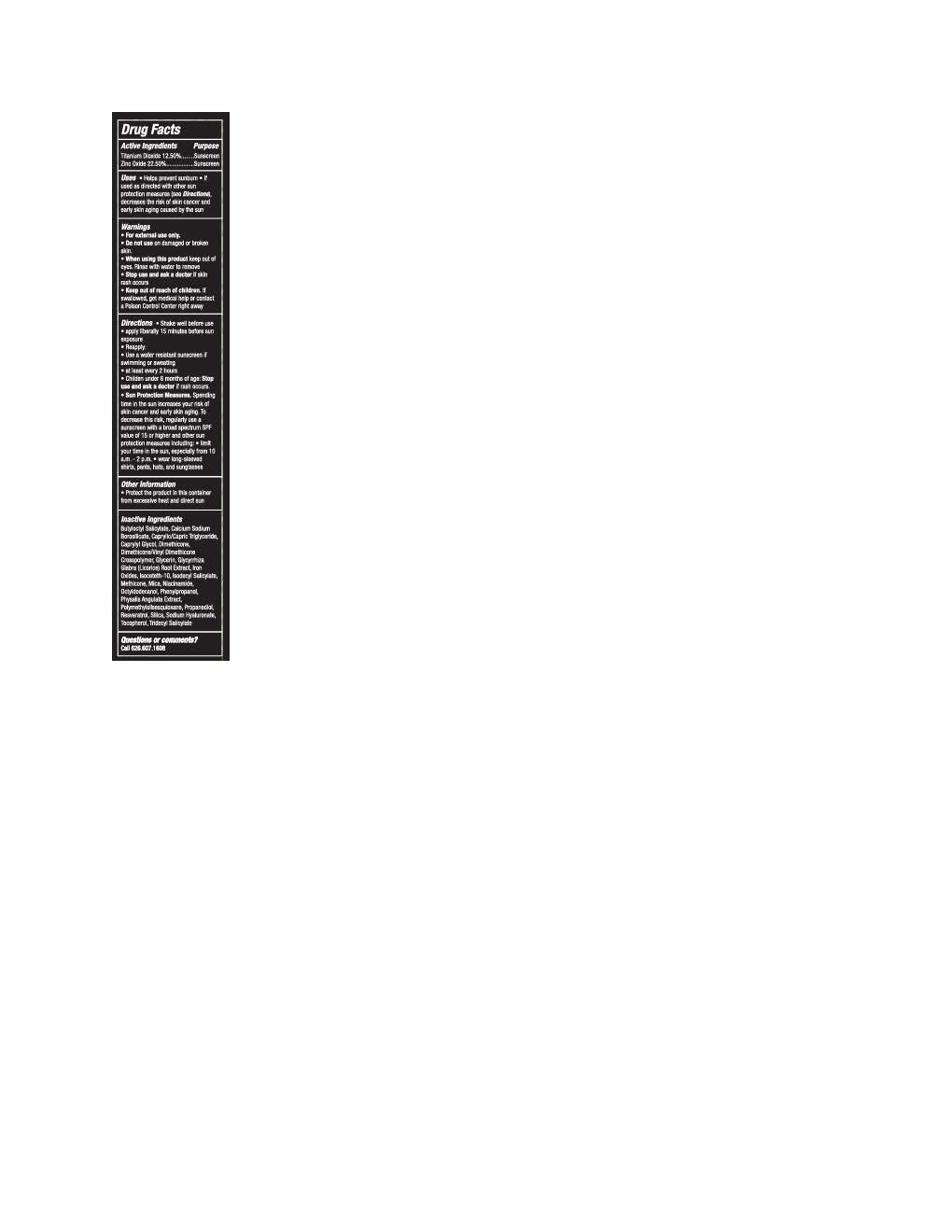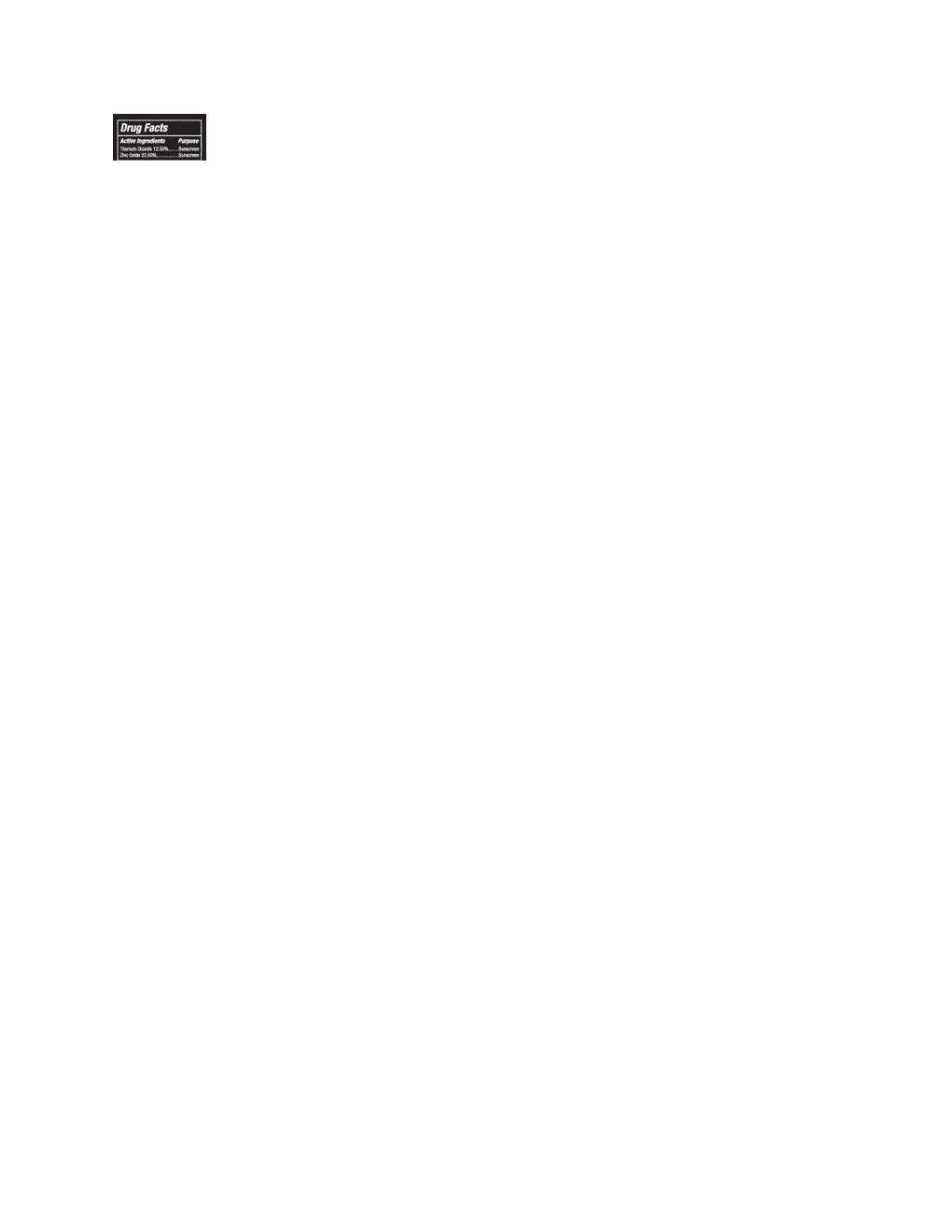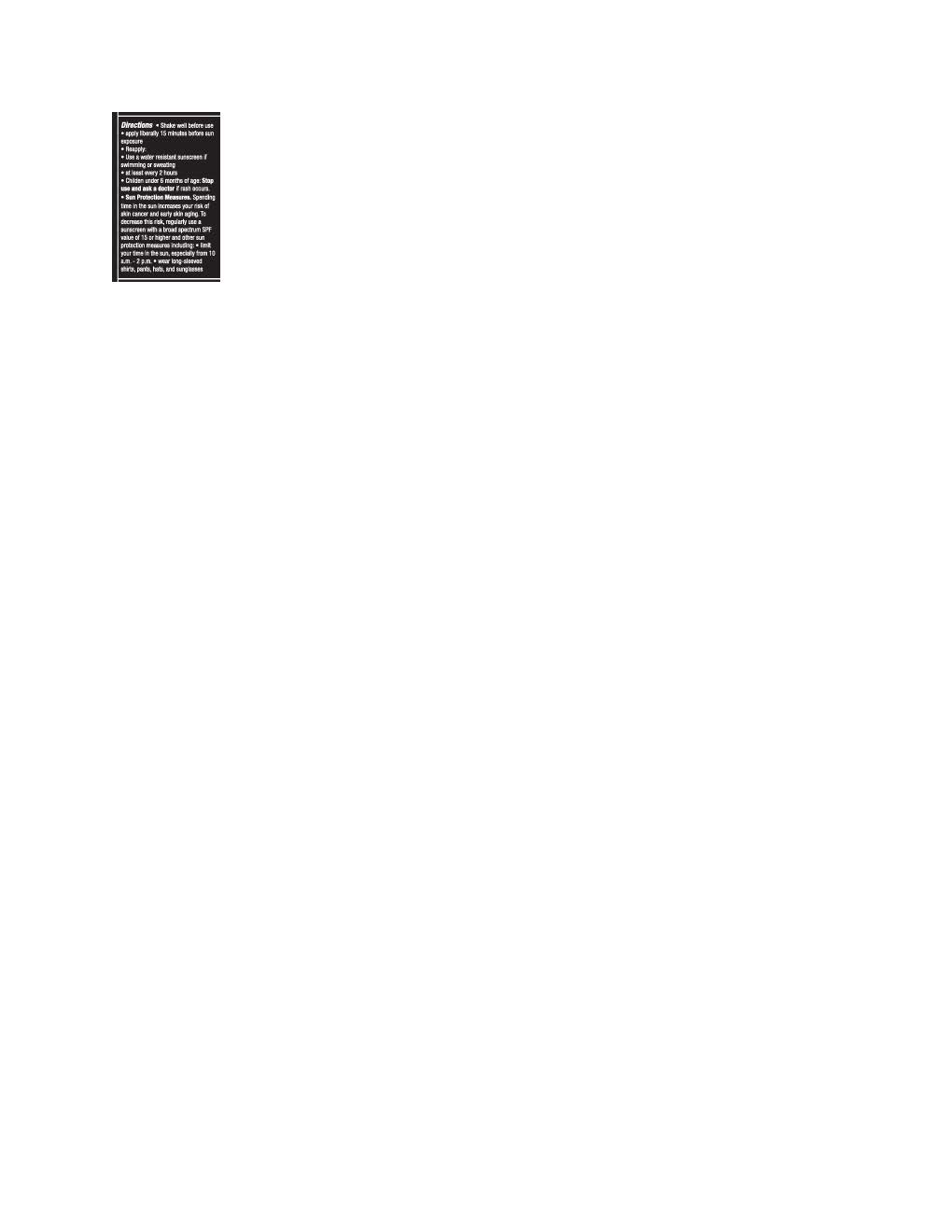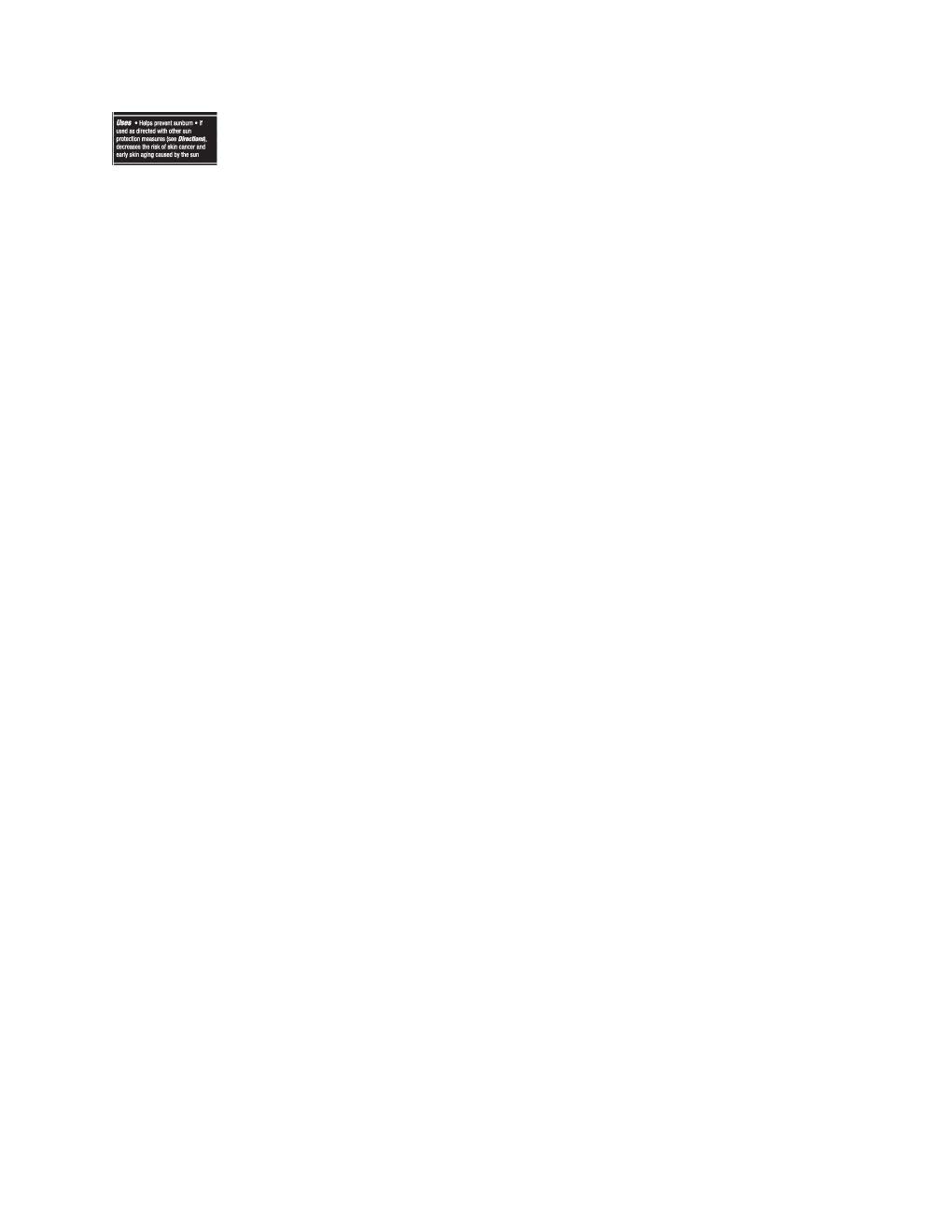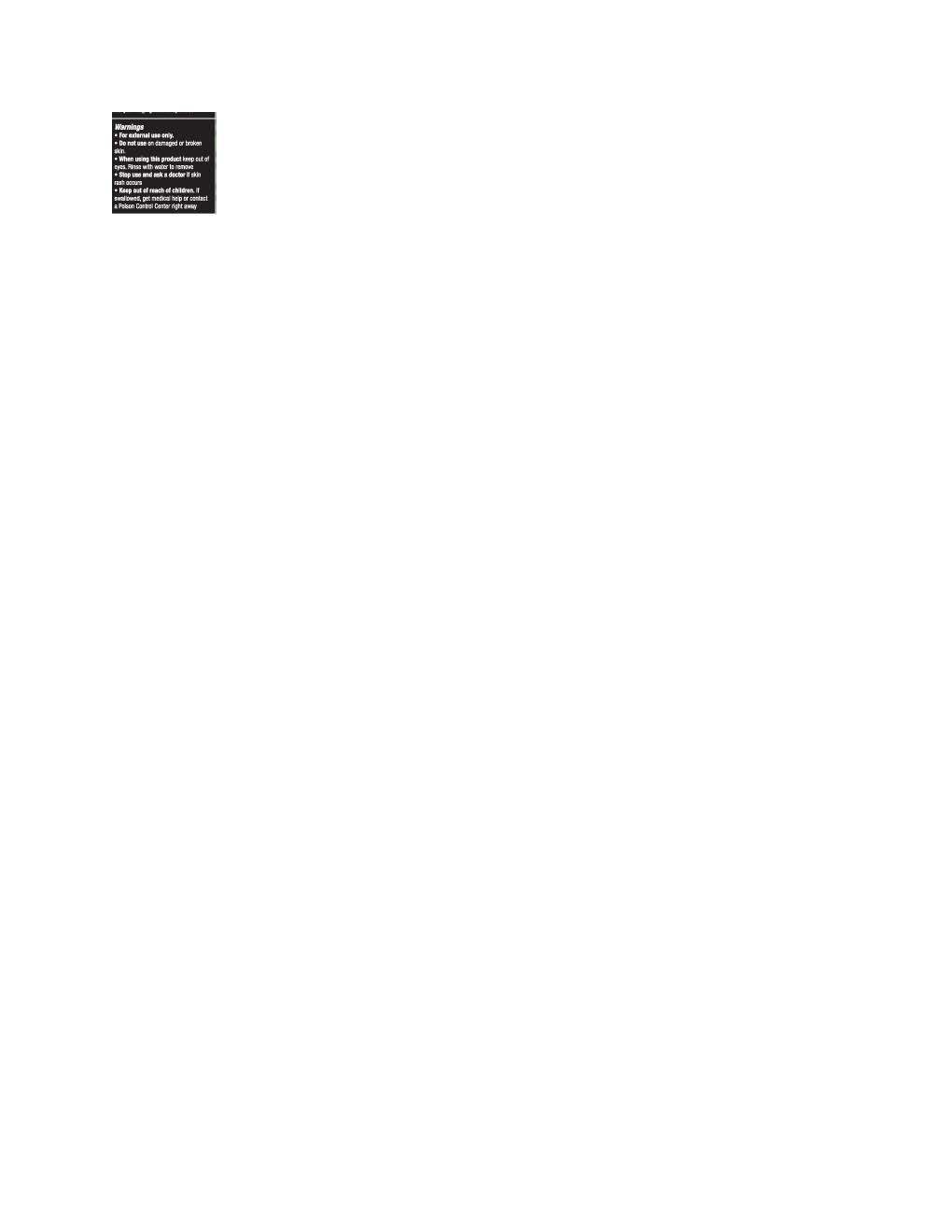 DRUG LABEL: DRMTLGY Radiance Powder
NDC: 83286-191 | Form: POWDER
Manufacturer: DRMTLGY
Category: otc | Type: HUMAN OTC DRUG LABEL
Date: 20250924

ACTIVE INGREDIENTS: TITANIUM DIOXIDE 0.125 g/1 g; ZINC OXIDE 0.225 g/1 g
INACTIVE INGREDIENTS: GLYCERIN; TRIDECYL SALICYLATE; OCTYLDODECANOL; ISOCETETH-10; PHENYLPROPANOL; METHICONE (20 CST); PHYSALIS ANGULATA; PROPANEDIOL; RESVERATROL; GLYCYRRHIZA GLABRA; BUTYLOCTYL SALICYLATE; CAPRYLYL GLYCOL; NIACINAMIDE; ISODECYL SALICYLATE; TOCOPHEROL; MICA; DIMETHICONE; POLYMETHYLSILSESQUIOXANE (11 MICRONS); DIMETHICONE/VINYL DIMETHICONE CROSSPOLYMER (SOFT PARTICLE); SILICON DIOXIDE

DRMTLGY Radiance Powder